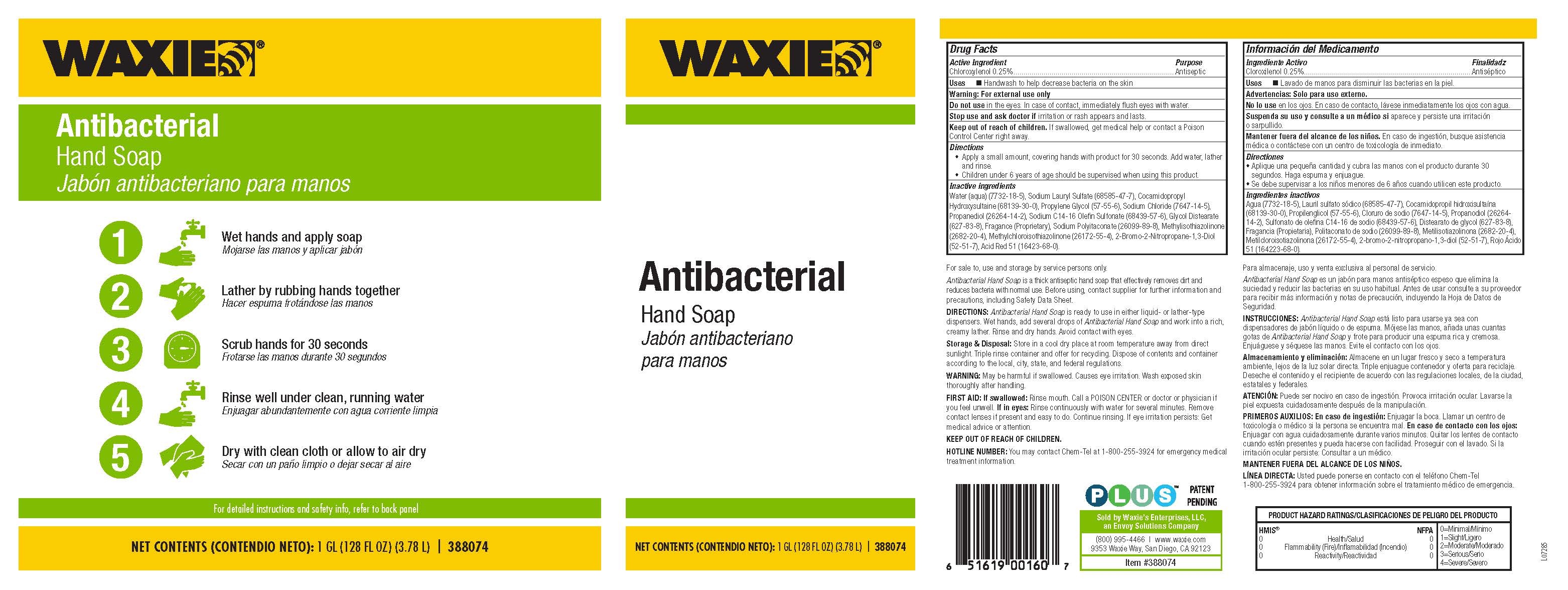 DRUG LABEL: Waxie Antibacterial Hand
NDC: 61666-901 | Form: SOAP
Manufacturer: Waxie's Enterprises, LLC
Category: otc | Type: HUMAN OTC DRUG LABEL
Date: 20250919

ACTIVE INGREDIENTS: CHLOROXYLENOL 2.5 g/1 L
INACTIVE INGREDIENTS: ACID RED 51; 2-BROMO-2-NITROPROPANE-1,3-DIOL; COCAMIDOPROPYL HYDROXYSULTAINE; METHYLCHLOROISOTHIAZOLINONE; PROPYLENE GLYCOL; METHYLISOTHIAZOLINONE; WATER; PROPANEDIOL; FRAGRANCE 13576; SODIUM CHLORIDE; SODIUM LAURYL SULFATE; SODIUM POLYITACONATE (2800 MW, PHOSPHATE TERMINATED); SODIUM C14-16 OLEFIN SULFONATE; GLYCOL DISTEARATE

Active Ingredient

Chloroxylenol 0.25%.

Purpose

Antiseptic

Uses

Handwash to help decrease bacteria on the skin

Warning:

For external use only

Do not use in the eyes. In case of contact, immediately flush eyes with water.

Stop use and ask doctor if irritation or rash appears and lasts.

Keep out of reach of children. If swallowed, get medical help or contact a Poison Control Center right away.

Directions

• Apply a small amount, covering hands with product for 30 seconds. Add water, lather and rinse.
• Children under 6 years of age should be supervised when using this product.

Inactive ingredients

Water (aqua) (7732-18-5), Sodium Lauryl Sulfate (68585-47-7), Cocamidopropyl Hydroxysultaine (68139-30-0), Propylene Glycol (57-55-6), Sodium Chloride (7647-14-5), Propanediol (26264-14-2), Sodium C14-16 Olefin Sulfonate (68439-57-6), Glycol Distearate (627-83-8), Fragance (Proprietary), Sodium Polyitaconate (26099-89-8), Methylisothiazolinone (2682-20-4), Methylchloroisothiazolinone (26172-55-4), 2-Bromo-2-Nitropropane-1,3-Diol (52-51-7), Acid Red 51 (16423-68-0).